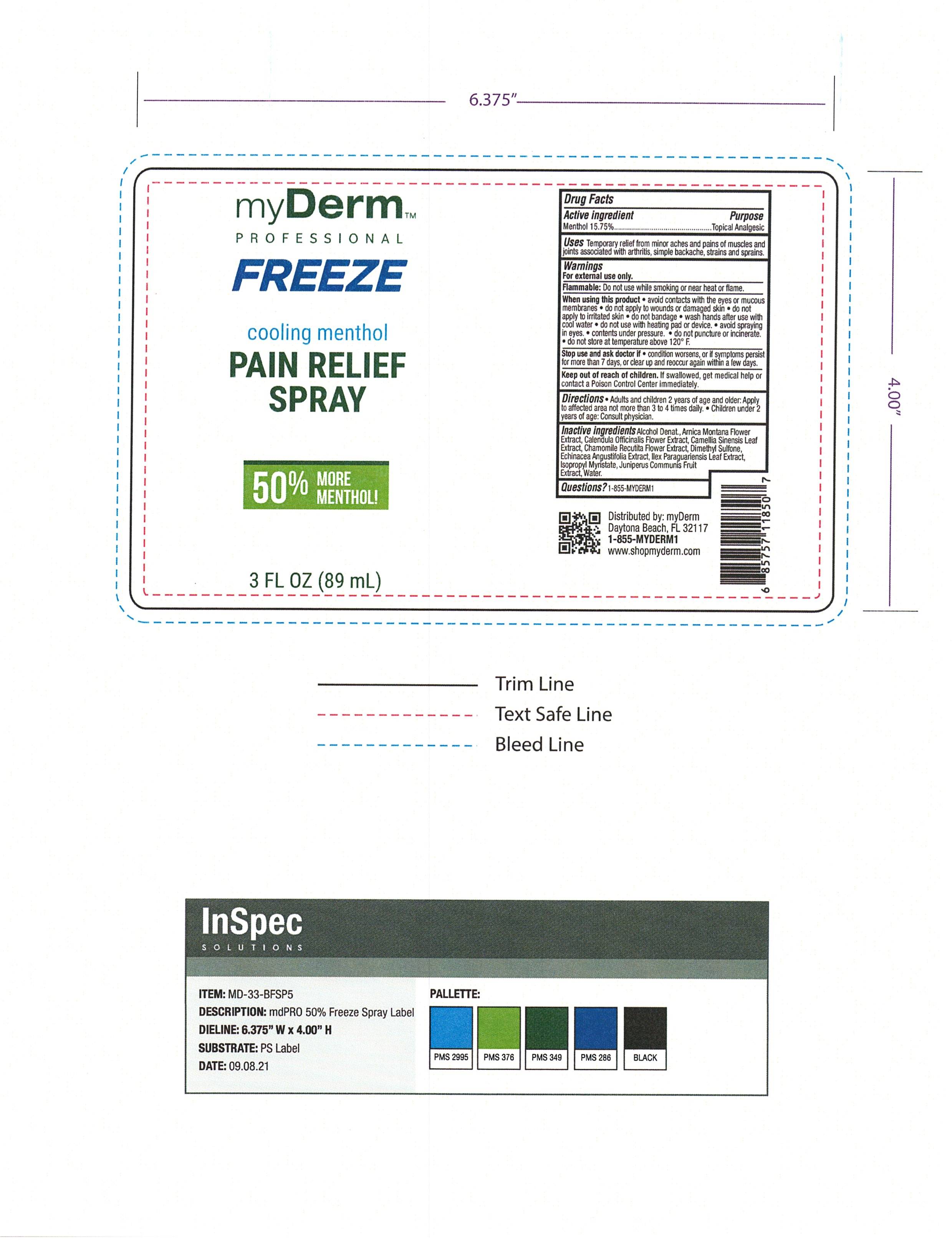 DRUG LABEL: myDerm Cooling Menthol Pain Relief with 50 Percent More Menthol
NDC: 72667-020 | Form: SPRAY
Manufacturer: Inspec Solutions LLC
Category: otc | Type: HUMAN OTC DRUG LABEL
Date: 20250131

ACTIVE INGREDIENTS: MENTHOL 15.75 g/100 mL
INACTIVE INGREDIENTS: FRANKINCENSE; FD&C YELLOW NO. 5; GLYCERIN; MELISSA OFFICINALIS LEAF; TROLAMINE; WATER; ALOE VERA LEAF; ARCTIUM LAPPA ROOT; ARNICA MONTANA FLOWER; ISOPROPYL MYRISTATE; ILEX PARAGUARIENSIS LEAF; CALENDULA OFFICINALIS FLOWER; GREEN TEA LEAF; CAMPHOR (NATURAL); CARBOMER 940; FD&C BLUE NO. 1; ISOPROPYL ALCOHOL; SILICON DIOXIDE; .ALPHA.-TOCOPHEROL ACETATE

myDerm Cooling Menthol Pain Relief Spray with 50% More Menthol

Active ingredient

Menthol 10.5%

PURPOSE

Menthol 10.4% ................. Topical Analgesic

INDICATIONS AND USAGE

Uses Temporary relief from minor aches and pains of muscles and joints associated with, arthritis, simple backache, strains, bruises, sprains.

WARNINGS

For external use only

When using this product, avoid contact with eyes and mucous membranes., do not apply to wound or damage skin, do not bandage, do not use with heating pad or device.

Stop use and ask a doctor if, condition worsens, symptoms persist for more than 7 days or clear up and occur again within a few days.

Keep out of reach of children, if swallowed, get medical help or contact a Poison Control Center right away.

DOSAGE AND ADMINISTRATION

Adults and children 2 years of age and older: Apply to affected area no more than 3 to 4 times daily. Wash hands with soap. Children under 2 years of age: consult a doctor.

INACTIVE INGREDIENTS

Aloe Barbadensis Leaf Extract

Arctium Lappa Root (Burdock) Extract

Arnica Montana Flower Extract

Boswellia Carterii Resin Extract

Calendula Officinalis Extract

Camellia Sinensis Leaf Extract

Camphor

Carbomer

FD&C Blue #1

FD&C Yellow #5

Full Spectrum Industrial Hemp Extract

Glycerin

Ilex Paraguariensis (Mate) Leaf Extract

Isopropyl Alcohol

Isopropyl Myristate

Melissa Officinalis (Lemon Balm) Leaf Extract

Silica

Tocopheryl Acetate

Triethanolamine

Water